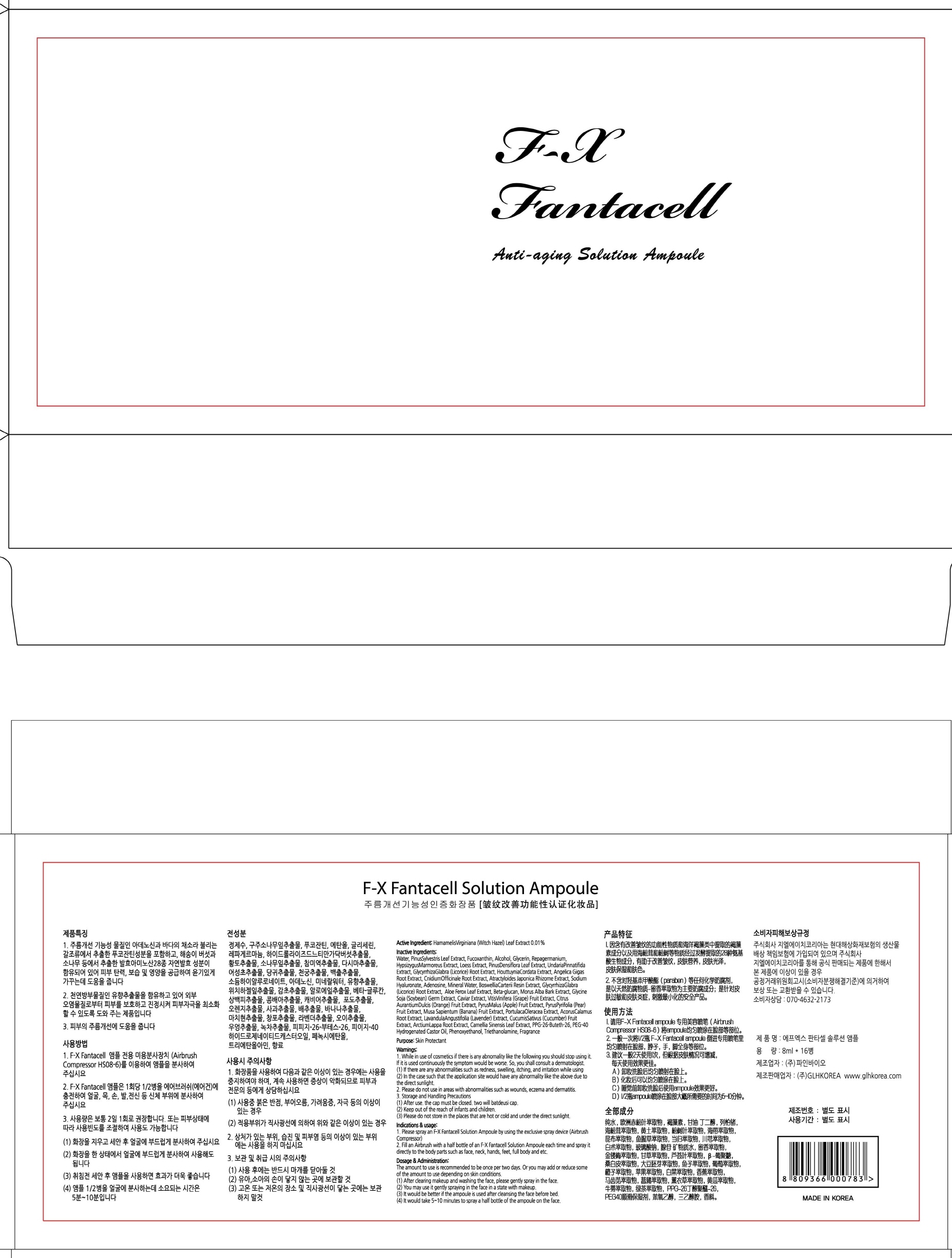 DRUG LABEL: F X Fantacell Ampoule
NDC: 71081-010 | Form: SOLUTION
Manufacturer: GLHKOREA
Category: otc | Type: HUMAN OTC DRUG LABEL
Date: 20161109

ACTIVE INGREDIENTS: Witch Hazel 0.8 mg/8 mL
INACTIVE INGREDIENTS: Water; Glycerin

ACTIVE INGREDIENT

Active Ingredient: Hamamelis Virginiana (Witch Hazel) Leaf Extract 0.01%

INACTIVE INGREDIENT

Inactive Ingredients: Water, Pinus Sylvestris Leaf Extract, Fucoxanthin, Alcohol, Glycerin, Repagermanium, Hypsizygus Marmoreus Extract, Loess Extract, Pinus Densiflora Leaf Extract, Undaria Pinnatifida Extract, Glycyrrhiza Glabra (Licorice) Root Extract, Houttuynia Cordata Extract, Angelica Gigas Root Extract, Cnidium Officinale Root Extract, Atractyloides Japonica Rhizome Extract, Sodium Hyaluronate, Adenosine, Mineral Water, Boswellia Carterii Resin Extract, Glycyrrhiza Glabra (Licorice) Root Extract, Aloe Ferox Leaf Extract, Beta-glucan, Morus Alba Bark Extract, Glycine Soja (Soybean) Germ Extract, Caviar Extract, Vitis Vinifera (Grape) Fruit Extract, Citrus Aurantium Dulcis (Orange) Fruit Extract, Pyrus Malus (Apple) Fruit Extract, Pyrus Pyrifolia (Pear) Fruit Extract, Musa Sapientum (Banana) Fruit Extract, Portulaca Oleracea Extract, Acorus Calamus Root Extract, Lavandula Angustifolia (Lavender) Extract, Cucumis Sativus (Cucumber) Fruit Extract, Arctium Lappa Root Extract, Camellia Sinensis Leaf Extract, PPG-26-Buteth-26, PEG-40 Hydrogenated Castor Oil, Phenoxyethanol, Triethanolamine, Fragrance

PURPOSE

Purpose: Skin Protectant

WARNINGS

Warnings: 1. While in use of cosmetics if there is any abnomality like the following you should stop using it. If it is used continuously the symptom would be worse. So, you shall consult a dermatologist. (1) If there are any abnormalities such as redness, swelling, itching, and irritation while using (2) In the case such that the application site would have any abnormality like the above due to the direct sunlight. 2. Please do not use in areas with abnormalities such as wounds, eczema and dermatitis. 3. Storage and Handling Precautions (1) After use. the cap must be closed. two will batdeusi cap. (2) Keep out of the reach of infants and children. (3) Please do not store in the places that are hot or cold and under the direct sunlight.

KEEP OUT OF REACH OF CHILDREN

Keep out of the reach of infants and children.

INDICATIONS & USAGE

Indications & usage: 1. Please spray an F-X Fantacell Solution Ampoule by using the exclusive spray device (Airbrush Compressor) 2. Fill an Airbrush with a half bottle of an F-X Fantacell Solution Ampoule each time and spray it directly to the body parts such as face, neck, hands, feet, full body and etc.

DOSAGE & ADMINISTRATION

Dosage & Administration: The amount to use is recommended to be once per two days. Or you may add or reduce some of the amount to use depending on skin conditions. (1) After clearing makeup and washing the face, please gently spray in the face. (2) You may use it gently spraying in the face in a state with makeup. (3) It would be better if the ampoule is used after cleansing the face before bed. (4) It would take 5~10 minutes to spray a half bottle of the ampoule on the face.